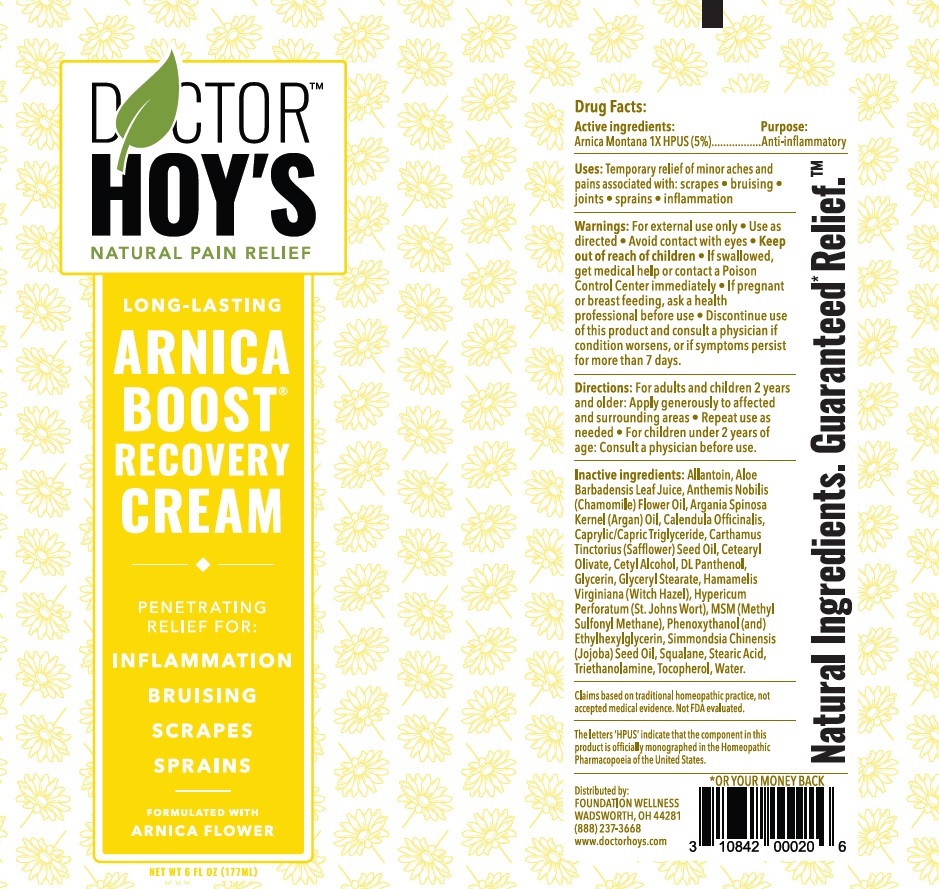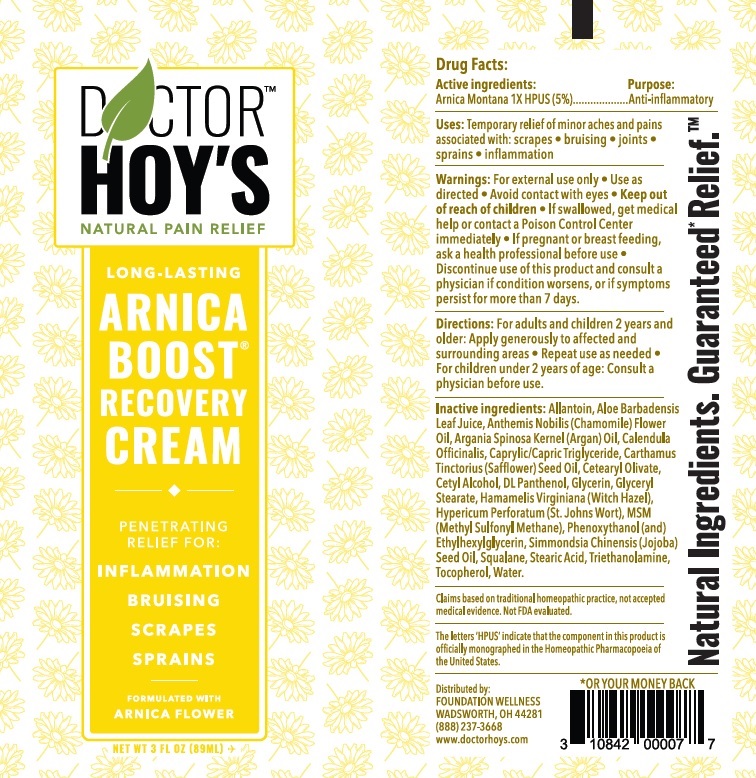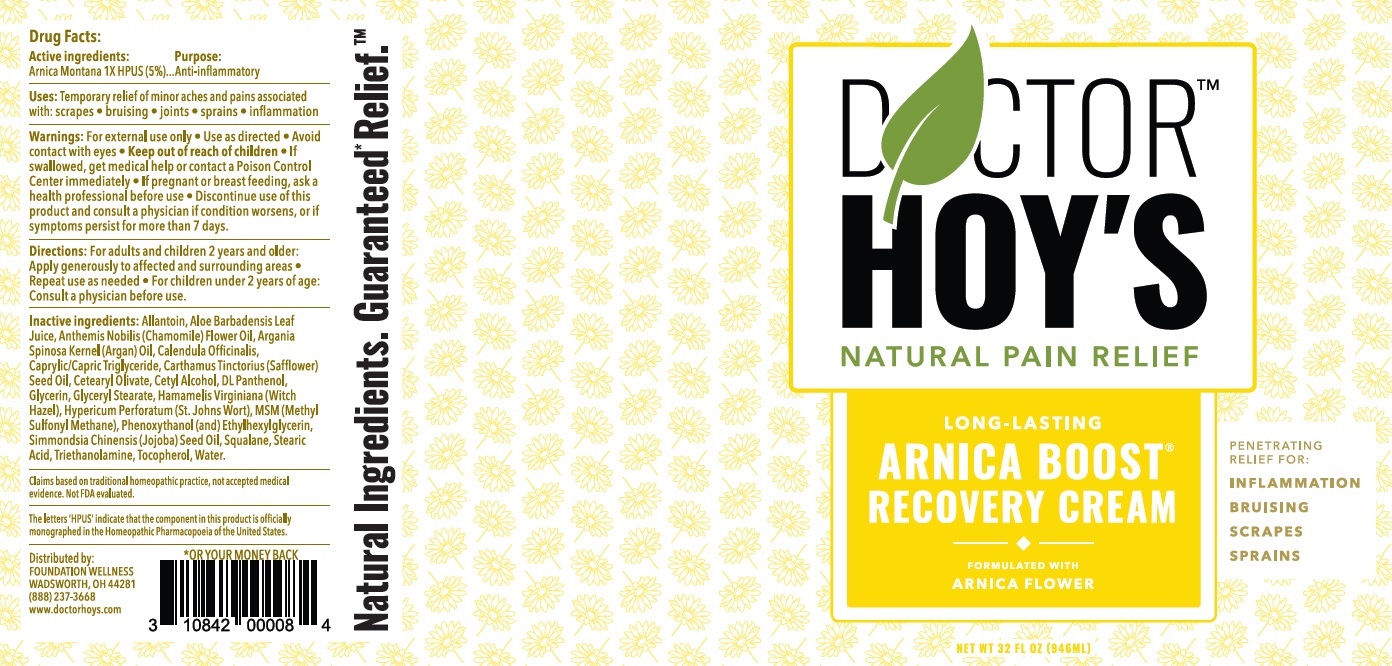 DRUG LABEL: Doctor Hoys Arnica Boost Recovery
NDC: 75638-009 | Form: GEL
Manufacturer: Dynamic Blending Specialists, Inc.
Category: homeopathic | Type: HUMAN OTC DRUG LABEL
Date: 20260102

ACTIVE INGREDIENTS: ARNICA MONTANA 50 mg/1 mL
INACTIVE INGREDIENTS: ALLANTOIN; ALOE VERA LEAF; CHAMAEMELUM NOBILE FLOWER OIL; ARGAN OIL; CALENDULA OFFICINALIS FLOWERING TOP; MEDIUM-CHAIN TRIGLYCERIDES; SAFFLOWER OIL; CETEARYL OLIVATE; CETYL ALCOHOL; PANTHENOL; GLYCERIN; GLYCERYL MONOSTEARATE; HAMAMELIS VIRGINIANA ROOT BARK/STEM BARK; HYPERICUM PERFORATUM WHOLE; DIMETHYL SULFONE; PHENOXYETHANOL; ETHYLHEXYLGLYCERIN; JOJOBA OIL; SQUALANE; STEARIC ACID; TROLAMINE; TOCOPHEROL; WATER

Doctor Hoy's Arnica Boost Recovery Cream

Active ingredients:

Arnica Montana 1X HPUS (5%)

Purpose:

Anit-inflammatory

Uses:

Temporary relief of minor aches and pains associated with: scrapes • bruising • joints • sprains • inflammation

Warnings:

• For external use only

• Use as directed

• Avoid contact with eyes

Keep Out of reach of children

If swallowed, get medical help or contact a Poison Control Center immediately

If pregnant or breast feeding,

• ask a health professional before use

• Discontinue use of this product and consult a physician if condition worsens, or if symptoms persist for more than 7 days.

Directions:

• For adults and children 2 years and older: Apply generously to affected and surrounding areas

• Repeat use as needed

• For children under 2 years of age: Consult a physician before use.

Inactive ingedients:

Aloe Barbadensis Leaf Juice, Anthemis Nobilis (Chamomile) Flower Oil, Argania Spinosa Kernel (Argan) Oil, Calendula Officinalis, Caprylic/Capric Triglyceride, Carthamus Tinctorius (Safflower) Seed Oil, Cetearyl Olivate, Cetyl Alcohol, DL Panthenol, Glycerin, Glyceryl Stearate, Hamamelis Virginiana (Witch Hazel), Hypericum Perforatum (St. Johns Wort), MSM (Methyl Sulfonyl Methane), Phenoxyethanol(and) Ethylhexylglycerin, Simmondsia Chinensis (Jojoba) Seed Oil, Squalane, Stearic Acid, Triethanolamine, Tocopherol, Water.